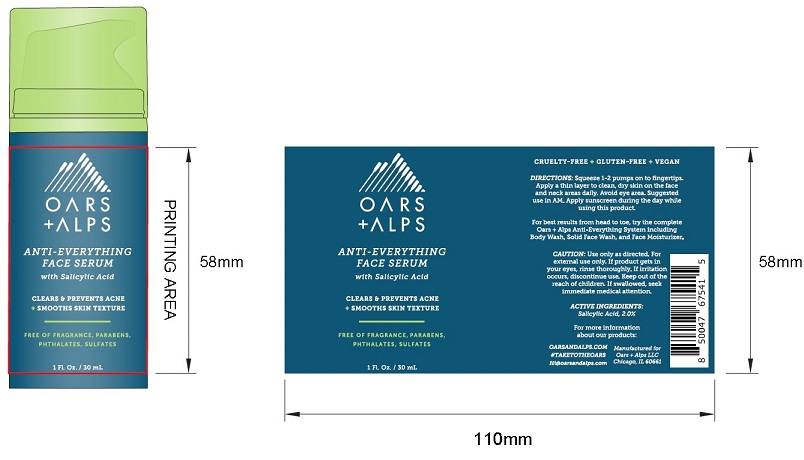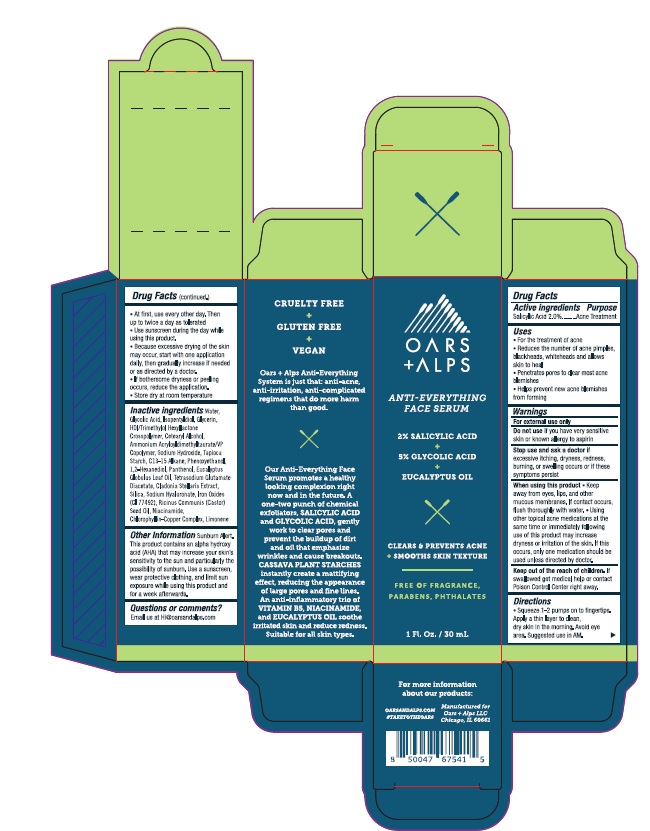 DRUG LABEL: Anti-Everything Face Serum
NDC: 54111-180 | Form: LIQUID
Manufacturer: Bentley laboratories, llC
Category: otc | Type: HUMAN OTC DRUG LABEL
Date: 20240805

ACTIVE INGREDIENTS: Salicylic Acid 2.0 g/100 mL
INACTIVE INGREDIENTS: WATER; GLYCOLIC ACID; ISOPENTYLDIOL; GLYCERIN; HEXAMETHYLENE DIISOCYANATE/TRIMETHYLOL HEXYLLACTONE CROSSPOLYMER; CETOSTEARYL ALCOHOL; AMMONIUM ACRYLOYLDIMETHYLTAURATE/VP COPOLYMER; SODIUM HYDROXIDE; STARCH, TAPIOCA; C13-15 ALKANE; PHENOXYETHANOL; 1,2-HEXANEDIOL; PANTHENOL; EUCALYPTUS OIL; TETRASODIUM GLUTAMATE DIACETATE; CLADONIA CRISTATELLA WHOLE; SILICON DIOXIDE; HYALURONATE SODIUM; FERRIC OXIDE YELLOW; CASTOR OIL; NIACINAMIDE; SODIUM COPPER CHLOROPHYLLIN; LIMONENE, (+)-

Oars + Alps Anti-Everything Face Serum

Drug Facts

Active Ingredients

Salicylic Acid 2.0%

Purpose

Acne Treatment

Uses
• For tha treatment of acne
• Reduces tha number of aena pimples,
blackheads, whiteheads and allows
skin to heal
• Pllnatrates paras to clear I110lIl acne
blemishes
• Helps prevent new acne blemishes
lromformlng

Warnings
For external use only

Do not use if you have very sensitive
skin or known allergy to aspirin

Slop use and ask a doctor if
excessive itching, dryness, redness,
burning, or swelling occurs or if these
symptoms persist

When ullng this product • Keep
away from eyes, lips, and other
mucous membranes. If contact occurs,
flush thoroughly with water.• Using
other topical acne medications at the
same time or immediately following
use of this product may increase
dryness or irritation of the skin. If this
occurs, only one medication should be
used unless directed by doctor.

Keep out of the reach of children. If
swallowed get medical help or contact
Poison Control Center right away.

Directions
• Squeeze 1-2 pumps on to fingertlps.
Apply a thin layer to clean,
dry skin in the morning. Avoid eye
area. Suggested use In AM.

• At first, use every other day. Then
up to twice a day as tolerated
• Use sunscreen during the day while
using this product
• Because excessive drying of the skin
may occur, start with one application
daily, then gradually increase if needed
or as directed by a doctor.
• If bothersome dryness or peeling
occurs, reduce the application.
• Store dry at room temperature

Inactive ingredients Water,
Glycolic Acid, Isopentyldiol, Glycerin,
HDI/Trimethylol Hexyllactone
Crosspolymer, Cetearyl Alcohol,
Ammonium Acryloyldimethyltaurate/VP
Copolymer, Sodium Hydroxide, Tapioca
Starch, C13-15 Alkane, Phenoxyethanol,
1,2-Hexanediol, Panthenol, Eucalyptus
Globulus Leaf Oil, Tetrasodium Glutamate
Diacetate, Cladonia Stellaris Extract,
Silica, Sodium Hyaluronate, Iron Oxides
(CI 77492), Ricinus Communis (Castor)
Seed Oil, Niacinamide,
Chlorophyllin-Copper Complex, Limonene

Other Information Sunburn Alert.
This product contains an alpha hydroxy
acid (AHA) that may increase your skin's
sensitivity to the sun and particularly the
possibility of sunburn. Use a sunscreen,
wear protective clothing, and limit sun
exposure while using this product and
for a week afterwards.

Questions or comments?

Email us at HI@oarsandalps.com

Product Packaging: OARS + ALPS ANTI-EVERYTHING FACE SERUM

OARS + ALPS

ANTI-EVERYTHING

FACE SERUM

2% SALICYLIC ACID

5% GLYCOLIC ACID

1 Fl. Oz. / 20 mL

Manufactured for

Oars + Alps LLC

Chicago, IL 60661

res 080624